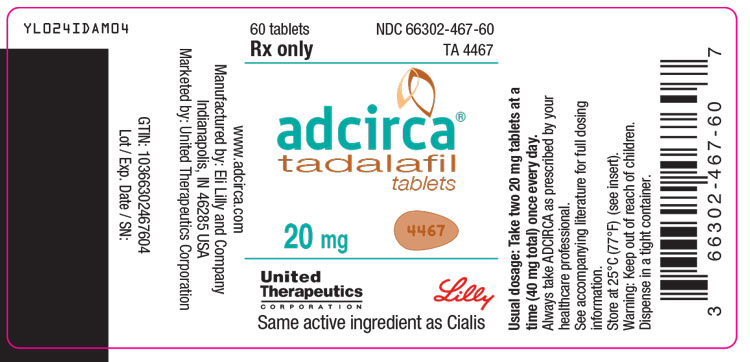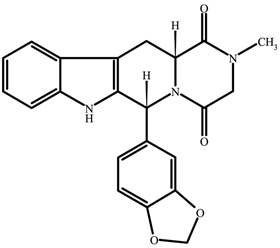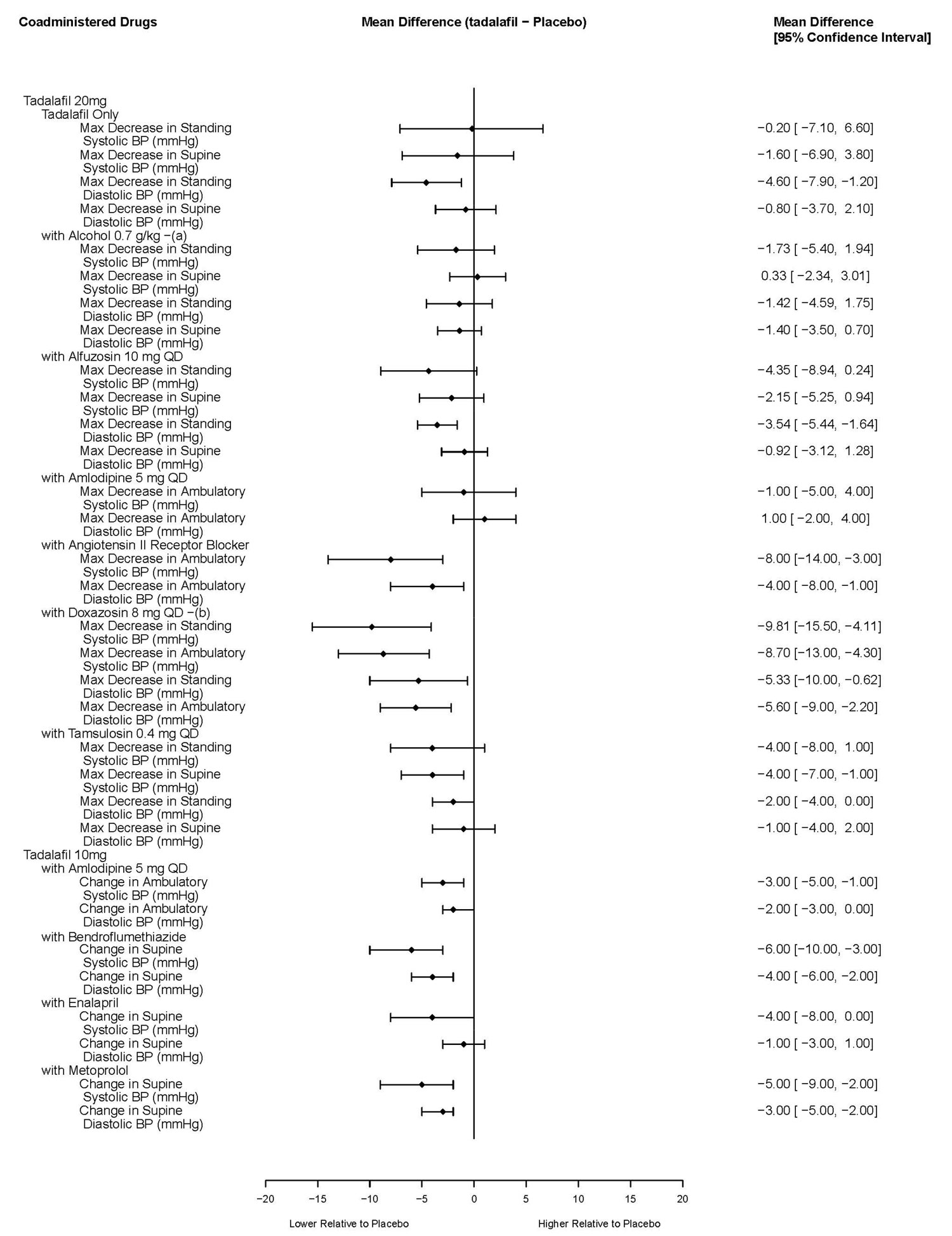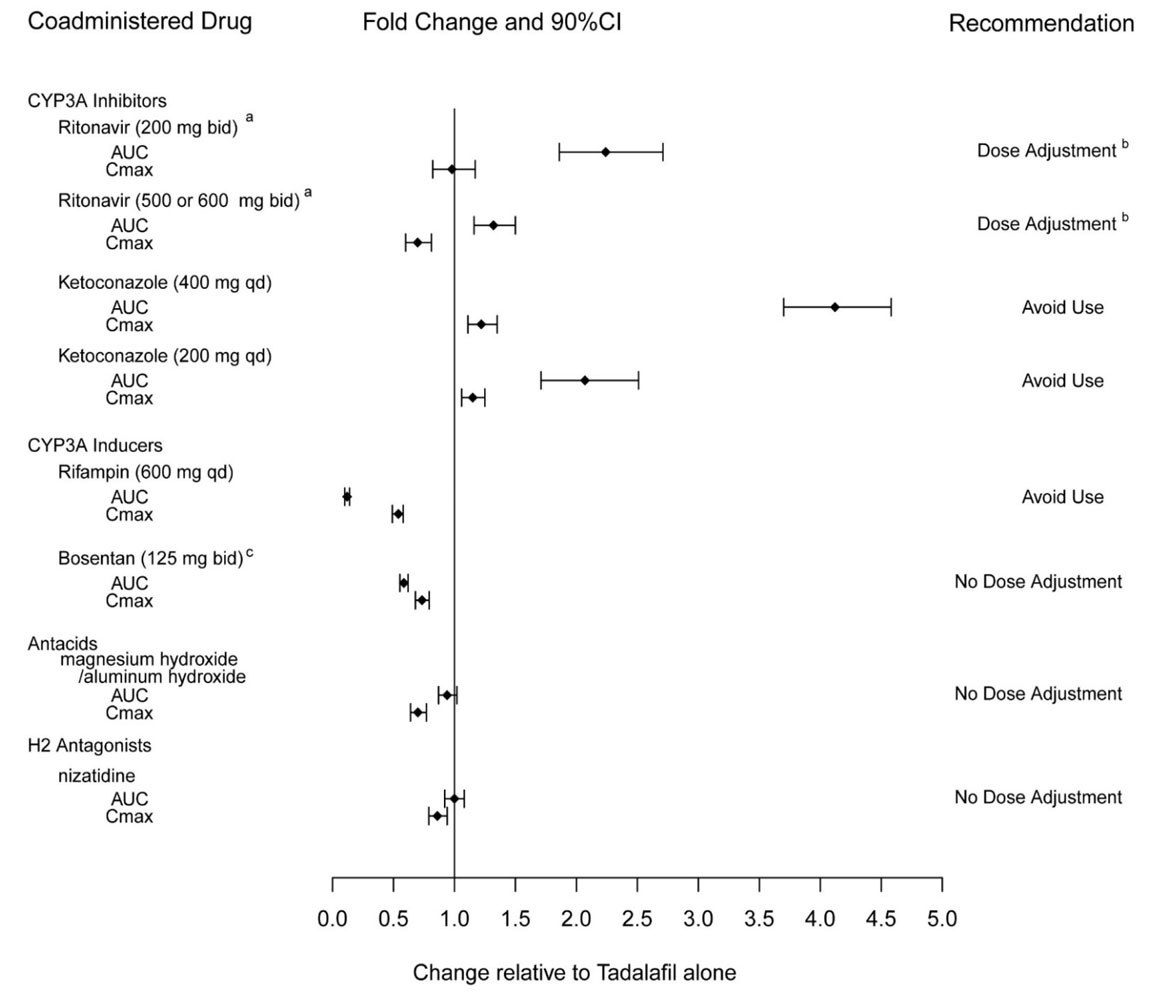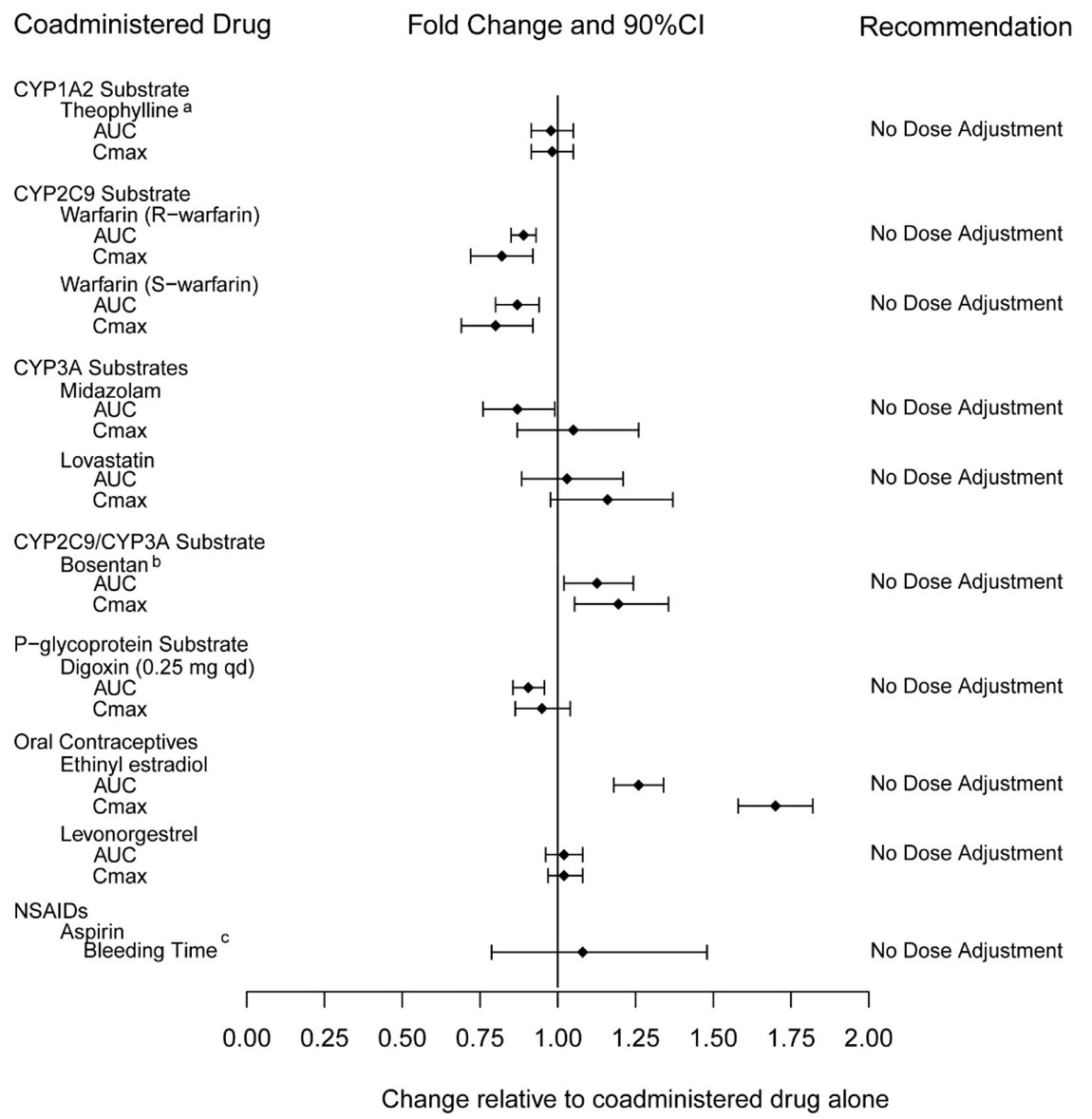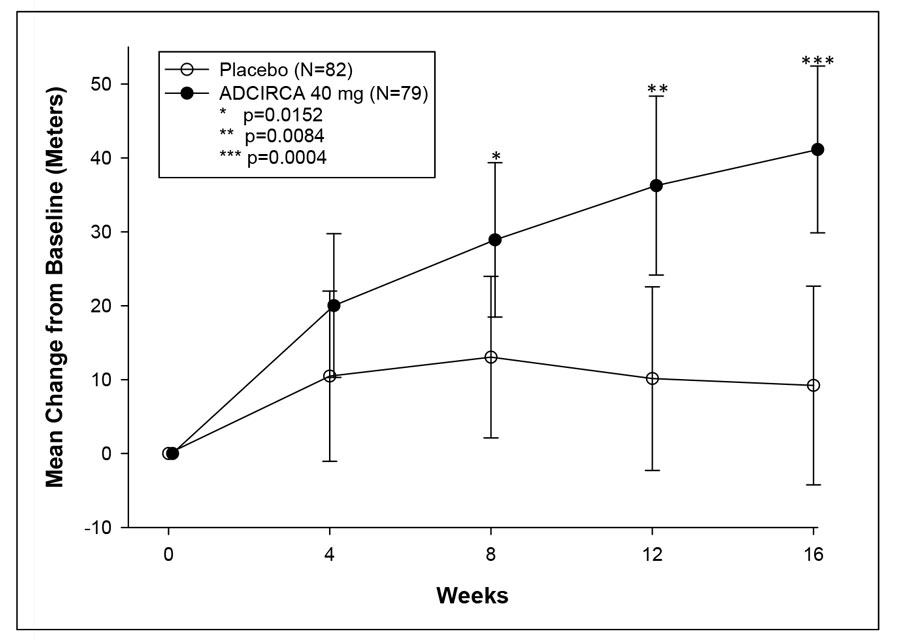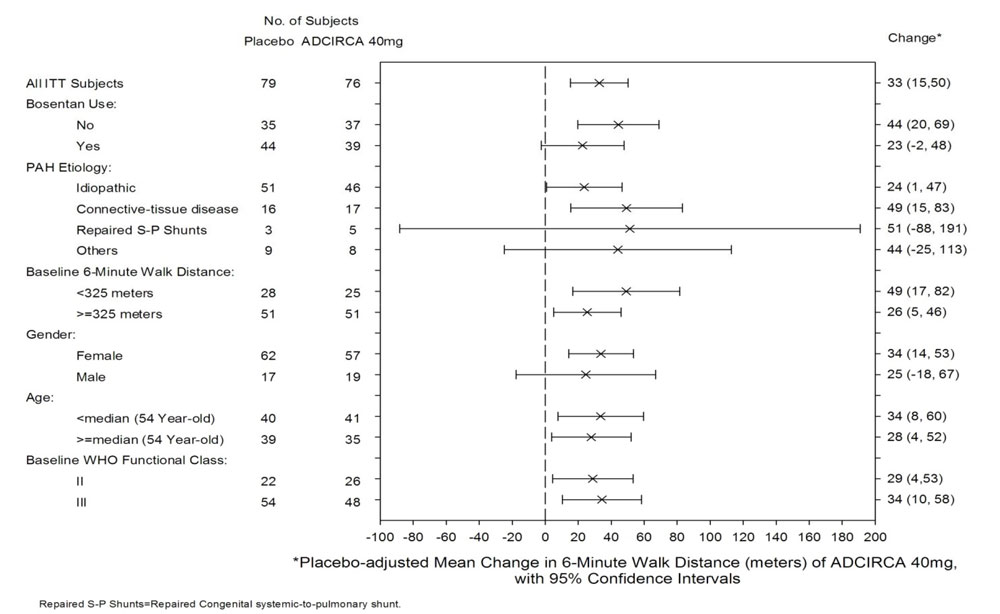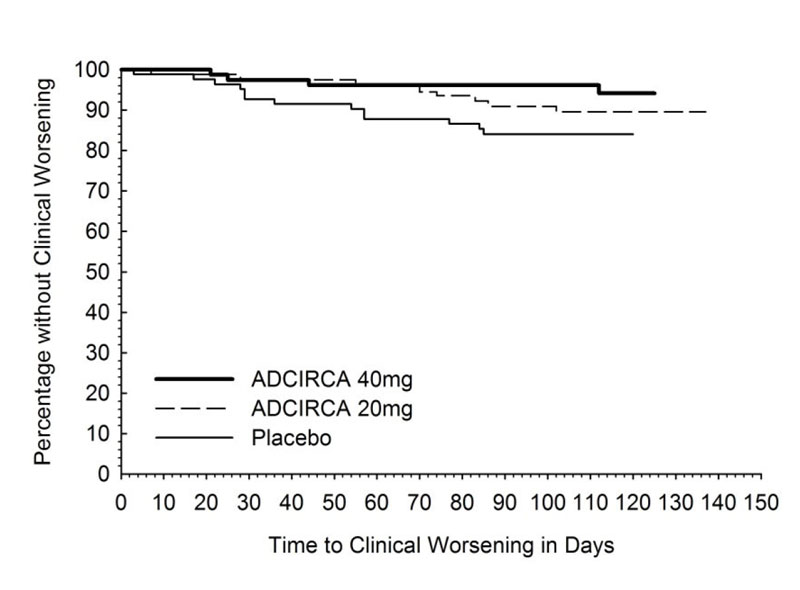 DRUG LABEL: ADCIRCA
NDC: 66302-467 | Form: TABLET
Manufacturer: United Therapeutics Corporation
Category: prescription | Type: HUMAN PRESCRIPTION DRUG LABEL
Date: 20251215

ACTIVE INGREDIENTS: Tadalafil 20 mg/1 1
INACTIVE INGREDIENTS: Croscarmellose sodium; Hydroxypropyl cellulose, Unspecified; Hypromellose, Unspecified; Microcrystalline cellulose; Lactose monohydrate; Magnesium stearate; Sodium lauryl sulfate; Talc; Titanium dioxide; Triacetin; Ferric oxide yellow; Ferric oxide red

HIGHLIGHTS OF PRESCRIBING INFORMATION

These highlights do not include all the information needed to use ADCIRCA safely and effectively. See full prescribing information for ADCIRCA.
ADCIRCA (tadalafil) tablets for oral administration
Initial U.S. Approval: 2003

1 INDICATIONS AND USAGE

ADCIRCA is a phosphodiesterase 5 (PDE5) inhibitor indicated for the treatment of pulmonary arterial hypertension (PAH) (WHO Group 1) to improve exercise ability. Studies establishing effectiveness included predominately patients with NYHA Functional Class II – III symptoms and etiologies of idiopathic or heritable PAH (61%) or PAH associated with connective tissue diseases (23%). (1.1)

2 DOSAGE AND ADMINISTRATION

- 40 mg once daily, with or without food. (2.1)
- Dividing the dose (40 mg) over the course of the day is not recommended. (2.1)
- Use with ritonavir requires dosage adjustments. (2.4)

3 DOSAGE FORMS AND STRENGTHS

Tablets (not scored): 20 mg (3)

4 CONTRAINDICATIONS

- Concomitant organic nitrates (4.1)
- Concomitant Guanylate Cyclase (GC) Stimulators (4.2)
- History of known serious hypersensitivity reaction to ADCIRCA or CIALIS (4.3)

5 WARNINGS AND PRECAUTIONS

- Hypotension: Carefully consider whether patients with certain underlying cardiovascular disease could be adversely affected by vasodilatory effects of ADCIRCA. Not recommended in patients with pulmonary veno-occlusive disease. (5.1, 5.2)
- Effects on the eye: Sudden loss of vision could be a sign of non-arteritic ischemic optic neuropathy (NAION) and may be permanent. (5.3)
- Hearing impairment: Cases of sudden decrease or loss of hearing have been reported with CIALIS. (5.4)
- Concomitant PDE5 inhibitors: Avoid use with CIALIS or other PDE5 inhibitors. (5.5)
- Prolonged erection: Advise patients to seek emergency treatment if an erection lasts >4 hours. (5.6)

6 ADVERSE REACTIONS

The most common adverse reaction is headache. (6.1)

To report SUSPECTED ADVERSE REACTIONS, contact Eli Lilly and Company at 1-800-545 5979 or FDA at 1-800-FDA-1088 or www.fda.gov/medwatch.

8 USE IN SPECIFIC POPULATIONS

Renal Impairment (2.2, 8.6, 12.3)

- Mild or moderate: Start with 20 mg once daily. (2.2, 8.6)
- Severe: Avoid use of ADCIRCA. (2.2, 8.6)

Hepatic Impairment (2.2, 8.7, 12.3)

- Mild or moderate: Consider starting dose of 20 mg once daily. (2.3, 8.7)
- Severe: Avoid use of ADCIRCA. (2.3, 8.7)

FULL PRESCRIBING INFORMATION

1 INDICATIONS AND USAGE

1.1 Pulmonary Arterial Hypertension

ADCIRCA® is indicated for the treatment of pulmonary arterial hypertension (PAH) (WHO Group 1) to improve exercise ability. Studies establishing effectiveness included predominately patients with NYHA Functional Class II – III symptoms and etiologies of idiopathic or heritable PAH (61%) or PAH associated with connective tissue diseases (23%).

2 DOSAGE AND ADMINISTRATION

2.1 Pulmonary Arterial Hypertension

The recommended dose of ADCIRCA is 40 mg (two 20 mg tablets) taken once daily with or without food. Dividing the dose (40 mg) over the course of the day is not recommended.

2.2 Dose Adjustment in Renal Impairment

Mild (creatinine clearance 51 to 80 mL/min) or moderate (creatinine clearance 31 to 50 mL/min): Start dosing at 20 mg once daily. Increase to 40 mg once daily based on individual tolerability.

Severe (creatinine clearance <30 mL/min and on hemodialysis): Avoid use of ADCIRCA because of increased tadalafil exposure (AUC), limited clinical experience, and the lack of ability to influence clearance by dialysis [see Use in Specific Populations (8.6)].

2.3 Dose Adjustment in Hepatic Impairment

Mild or moderate (Child Pugh Class A or B): Because of limited clinical experience in patients with mild to moderate hepatic cirrhosis, consider a starting dose of 20 mg once per day.

Severe (Child Pugh Class C): Patients with severe hepatic cirrhosis have not been studied. Avoid use of ADCIRCA [see Use in Specific Populations (8.7)].

2.4 Dose Adjustments for Use with Ritonavir

Co-administration of ADCIRCA in Patients on Ritonavir

In patients receiving ritonavir for at least one week, start ADCIRCA at 20 mg once daily. Increase to 40 mg once daily based upon individual tolerability [see Drug Interactions (7.5) and Clinical Pharmacology (12.3)].

Co-administration of Ritonavir in Patients on ADCIRCA

Avoid use of ADCIRCA during the initiation of ritonavir. Stop ADCIRCA at least 24 hours prior to starting ritonavir. After at least one week following the initiation of ritonavir, resume ADCIRCA at 20 mg once daily. Increase to 40 mg once daily based upon individual tolerability [see Drug Interactions (7.5) and Clinical Pharmacology (12.3)].

3 DOSAGE FORMS AND STRENGTHS

20 mg, orange, film-coated, almond-shaped tablets (not scored) debossed with “4467”.

4 CONTRAINDICATIONS

4.1 Concomitant Organic Nitrates

ADCIRCA is contraindicated in patients who are using any form of organic nitrate, either regularly or intermittently. Do not use nitrates within 48 hours of the last dose of ADCIRCA. ADCIRCA potentiates the hypotensive effect of nitrates. This potentiation is thought to result from the combined effects of nitrates and ADCIRCA on the nitric oxide/cGMP pathway [see Clinical Pharmacology (12.2)].

4.2 Concomitant Guanylate Cyclase (GC) Stimulators

Coadministration of GC stimulators such as riociguat with ADCIRCA is contraindicated. ADCIRCA may potentiate the hypotensive effects of GC stimulators.

4.3 Hypersensitivity Reactions

ADCIRCA is contraindicated in patients with a known serious hypersensitivity to tadalafil (ADCIRCA or CIALIS). Hypersensitivity reactions have been reported, including Stevens-Johnson syndrome and exfoliative dermatitis [see Adverse Reactions (6.2)].

5 WARNINGS AND PRECAUTIONS

5.1 Hypotension

ADCIRCA has vasodilatory properties that may result in transient decreases in blood pressure. Prior to prescribing ADCIRCA, carefully consider whether patients with underlying cardiovascular disease could be affected adversely by such vasodilatory effects. Patients with preexisting hypotension, with autonomic dysfunction, with left ventricular outflow obstruction, may be particularly sensitive to the actions of vasodilators.

5.2 Worsening Pulmonary Vascular Occlusive Disease

Pulmonary vasodilators may significantly worsen the cardiovascular status of patients with pulmonary veno-occlusive disease (PVOD). Since there are no clinical data on administration of ADCIRCA to patients with veno-occlusive disease, administration of ADCIRCA to such patients is not recommended. Should signs of pulmonary edema occur when ADCIRCA is administered, the possibility of associated PVOD should be considered.

5.3 Visual Loss

When used to treat erectile dysfunction, non-arteritic anterior ischemic optic neuropathy (NAION), a cause of decreased vision including permanent loss of vision, has been reported postmarketing in temporal association with the use of phosphodiesterase type 5 (PDE-5) inhibitors, including tadalafil. Most, but not all, of these patients had underlying anatomic or vascular risk factors for development of NAION, including but not necessarily limited to: low cup to disc ratio (“crowded disc”), age over 50, diabetes, hypertension, coronary artery disease, hyperlipidemia, and smoking. Based on published literature, the annual incidence of NAION is 2.5-11.8 cases per 100,000 in males aged ≥50 in the general population. An observational case-crossover study evaluated the risk of NAION when PDE5 inhibitor use, as a class, typical of erectile dysfunction treatment, occurred immediately before NAION onset (within 5 half-lives), compared to PDE5 inhibitor use in a prior time period. The results suggest an approximate 2-fold increase in the risk of NAION, with a risk estimate of 2.15 (95% CI 1.06, 4.34). A similar study reported a consistent result, with a risk estimate of 2.27 (95% CI 0.99, 5.20). Other risk factors for NAION, such as the presence of “crowded” optic disc, may have contributed to the occurrence of NAION in these studies.

Patients with known hereditary degenerative retinal disorders, including retinitis pigmentosa, were not included in the clinical trials, and use in these patients is not recommended.

5.4 Hearing Impairment

Cases of sudden decrease or loss of hearing, which may be accompanied by tinnitus and dizziness, have been reported in patients taking tadalafil. It is not possible to determine whether these events are related directly to the use of PDE5 inhibitors or to other factors [see Adverse Reactions (6.2)].

5.5 Combination with Other PDE5 Inhibitors

Tadalafil is also marketed for erectile dysfunction. The safety and efficacy of taking ADCIRCA together with another PDE5 inhibitor has not been studied. Inform patients taking ADCIRCA not to take other PDE5 inhibitors.

5.6 Prolonged Erection

There have been reports of prolonged erections greater than 4 hours and priapism (painful erections greater than 6 hours in duration) for this class of compounds. Patients with conditions that might predispose them to priapism (such as sickle cell anemia, multiple myeloma, or leukemia), or in patients with anatomical deformation of the penis (such as angulation, cavernosal fibrosis, or Peyronie's disease) are at an increased risk. Priapism, if not treated promptly, can result in irreversible damage to the erectile tissue. Patients who have an erection lasting greater than 4 hours, whether painful or not, should seek emergency medical attention.

6 ADVERSE REACTIONS

The following serious adverse reactions are discussed elsewhere in the labeling:

- Hypotension [see Warnings and Precautions (5.1)]
- Visual Loss [see Warnings and Precautions (5.3) and Patient Counseling Information (17)]
- Hearing loss [see Warnings and Precautions (5.4)]
- Priapism [see Warnings and Precautions (5.6)]

6.1 Clinical Trials Experience

Because clinical trials are conducted under widely varying conditions, adverse reaction rates observed in the clinical trials of a drug cannot be directly compared to rates in the clinical trials of another drug and may not reflect the rates observed in practice.

Tadalafil was administered to 398 patients with PAH during clinical trials worldwide. In trials of ADCIRCA, a total of 311 and 251 subjects have been treated for at least 182 days and 360 days, respectively. The overall rates of discontinuation because of an adverse event (AE) in the placebo-controlled trial were 9% for ADCIRCA 40 mg and 15% for placebo. The rates of discontinuation because of AEs, other than those related to worsening of PAH, in patients treated with ADCIRCA 40 mg was 4% compared to 5% in placebo-treated patients.

In the placebo-controlled study, the most common AEs were generally transient and mild to moderate in intensity. Table 1 presents treatment-emergent adverse events reported by ≥9% of patients in the ADCIRCA 40 mg group and occurring more frequently than with placebo.

Table 1: Treatment-Emergent Adverse Events Reported by ≥9% of Patients in ADCIRCA and More Frequent than Placebo by 2%
EVENT | Placebo (%) (N=82) | ADCIRCA 20 mg (%) (N=82) | ADCIRCA 40 mg (%) (N=79)
Headache | 15 | 32 | 42
Myalgia | 4 | 9 | 14
Nasopharyngitis | 7 | 2 | 13
Flushing | 2 | 6 | 13
Respiratory Tract Infection (Upper and Lower) | 6 | 7 | 13
Pain in Extremity | 2 | 5 | 11
Nausea | 6 | 10 | 11
Back Pain | 6 | 12 | 10
Dyspepsia | 2 | 13 | 10
Nasal Congestion (Including sinus congestion) | 1 | 0 | 9

6.2 Postmarketing Experience

The following adverse reactions have been identified during post-approval use of tadalafil. These events have been chosen for inclusion either because of their seriousness, reporting frequency, lack of clear alternative causation, or a combination of these factors. Because these reactions are reported voluntarily from a population of uncertain size, it is not always possible to estimate reliably their frequency or establish a causal relationship to drug exposure. The list does not include adverse events that are reported from clinical trials and that are listed elsewhere in this section.

Cardiovascular and cerebrovascular — Serious cardiovascular events, including myocardial infarction, sudden cardiac death, stroke, chest pain, palpitations, and tachycardia, have been reported postmarketing in temporal association with the use of tadalafil [see Contraindications (4.1)]. Most, but not all, of these patients had preexisting cardiovascular risk factors. Many of these events were reported to occur during or shortly after sexual activity, and a few were reported to occur shortly after the use of tadalafil without sexual activity. Others were reported to have occurred hours to days after the use of tadalafil and sexual activity. It is not possible to determine whether these events are related directly to tadalafil, to sexual activity, to the patient's underlying cardiovascular disease, to a combination of these factors, or to other factors.

Body as a whole — Hypersensitivity reactions including urticaria, Stevens–Johnson syndrome, and exfoliative dermatitis

Nervous — Migraine, seizure and seizure recurrence, and transient global amnesia

Ophthalmologic — Visual field defect, retinal vein occlusion, retinal artery occlusion, and NAION [see Warnings and Precautions (5.3) and Patient Counseling Information (17)].

Otologic — Cases of sudden decrease or loss of hearing have been reported postmarketing in temporal association with the use of PDE5 inhibitors, including tadalafil. In some of the cases, medical conditions and other factors were reported that may have also played a role in the otologic adverse events. In many cases, medical follow-up information was limited. It is not possible to determine whether these reported events are related directly to the use of tadalafil, to the patient's underlying risk factors for hearing loss, a combination of these factors, or to other factors [see Warnings and Precautions (5.4) and Patient Counseling Information (17)].

Urogenital — Priapism [see Warnings and Precautions (5.6)].

7 DRUG INTERACTIONS

7.1 Nitrates

Administration of nitrates within 48 hours after the last dose of ADCIRCA is contraindicated [see Contraindications (4.1)].

7.2 Alpha-Blockers

PDE5 inhibitors, including ADCIRCA, and alpha–adrenergic blocking agents are both vasodilators with blood-pressure-lowering effects. When vasodilators are used in combination, an additive effect on blood pressure may be anticipated. Clinical pharmacology studies have been conducted with coadministration of tadalafil with doxazosin, alfuzosin or tamsulosin [see Clinical Pharmacology (12.2)].

7.3 Antihypertensives

PDE5 inhibitors, including ADCIRCA, are mild systemic vasodilators. Clinical pharmacology studies were conducted to assess the effect of tadalafil on the potentiation of the blood–pressure–lowering effects of selected antihypertensive medications (amlodipine, angiotensin II receptor blockers, bendroflumethiazide, enalapril, and metoprolol). Small reductions in blood pressure occurred following coadministration of tadalafil with these agents compared with placebo [see Clinical Pharmacology (12.2)].

7.4 Alcohol

Both alcohol and tadalafil, a PDE5 inhibitor, act as mild vasodilators. When mild vasodilators are taken in combination, blood pressure–lowering effects of each individual compound may be increased. Substantial consumption of alcohol (e.g., 5 units or greater) in combination with ADCIRCA can increase the potential for orthostatic signs and symptoms, including increase in heart rate, decrease in standing blood pressure, dizziness, and headache. Tadalafil (10 mg or 20 mg) did not affect alcohol plasma concentrations and alcohol did not affect tadalafil plasma concentrations. [See Clinical Pharmacology (12.2)].

7.5 CYP3A Inhibitors/Inducers

Ritonavir

Ritonavir initially inhibits and later induces CYP3A, the enzyme involved in the metabolism of tadalafil. At steady state of ritonavir (about 1 week), the exposure to tadalafil is similar as in the absence of ritonavir [see Dosage and Administration (2.4) and Clinical Pharmacology (12.3)].

Potent Inhibitors of CYP3A

Tadalafil is metabolized predominantly by CYP3A in the liver. In patients taking potent inhibitors of CYP3A such as ketoconazole, and itraconazole, avoid use of ADCIRCA [see Clinical Pharmacology (12.3)].

Potent Inducers of CYP3A

For patients chronically taking potent inducers of CYP3A, such as rifampin, avoid use of ADCIRCA [see Clinical Pharmacology (12.3)].

8 USE IN SPECIFIC POPULATIONS

8.1 Pregnancy

Risk Summary

Limited data from case series with tadalafil use in pregnant women have not identified a drug-associated risk of major birth defects, miscarriage or adverse maternal or fetal outcomes. In animal reproduction studies, no adverse developmental effects were observed with oral administration of tadalafil to pregnant rats or mice during organogenesis at exposures 7 times the exposure at the maximum recommended human dose (MRHD) of 40 mg/day based on AUC (see Data).

The estimated background risk of major birth defects and miscarriage for the indicated population is unknown. All pregnancies have a background risk of birth defect, loss, or other adverse outcomes. In the U.S. general population, the background risk of major birth defects and miscarriage in clinically recognized pregnancies is 2-4% and 15- 20%, respectively.

Clinical Considerations

Disease-Associated Maternal and/or Embryo/Fetal Risk

Pregnant women with untreated pulmonary arterial hypertension are at risk for heart failure, stroke, preterm delivery, and maternal and fetal death.

Data

Animal Data

Tadalafil and/or its metabolites cross the placenta, resulting in fetal exposure in rats.

Animal reproduction studies showed no evidence of teratogenicity, embryotoxicity, or fetotoxicity when tadalafil was given to pregnant rats or mice at unbound tadalafil exposures up to 7 times the exposure at the maximum recommended human dose (MRHD) of 40 mg/day during organogenesis based on AUC. In one of two perinatal/postnatal developmental studies in rats, a reduction of postnatal pup survival was observed at dose levels of 60, 200 and 1000 mg/kg. The no-observed-effect-level (NOEL) for developmental toxicity was 30 mg/kg, which provided maternal exposure to unbound tadalafil concentrations approximately 5 times the exposure at the MRHD based on AUC. Signs of maternal toxicity occurred at doses greater than 200 mg/kg/day, which produced AUCs greater than 8 times the exposure at the MRHD. Surviving offspring had normal development and reproductive performance.

8.2 Lactation

Risk Summary

There are no data on the presence of tadalafil and/or its metabolites in human milk, the effects on the breastfed child, or the effects on milk production. Tadalafil and/or its metabolites are present in the milk of lactating rats at concentrations approximately 2.4-times that found in the plasma. When a drug is present in animal milk, it is likely that the drug will be present in human milk.

The developmental and health benefits of breastfeeding should be considered along with the mother's clinical need for ADCIRCA and any potential adverse effects on the breastfed child from ADCIRCA or from the underlying maternal condition.

8.3 Females and Males of Reproductive Potential

Infertility

Males

Based on the data from 3 studies in adult males, tadalafil decreased sperm concentrations in the study of 10 mg tadalafil for 6 months and the study of 20 mg tadalafil for 9 months. This effect was not seen in the study of 20 mg tadalafil taken for 6 months. There was no adverse effect of tadalafil 10 mg or 20 mg on mean concentrations of testosterone, luteinizing hormone or follicle stimulating hormone. The clinical significance of the decreased sperm concentrations in the two studies is unknown. There have been no studies evaluating the effect of tadalafil on fertility in men or women [see Clinical Pharmacology (12.2)].

8.4 Pediatric Use

Safety and effectiveness of ADCIRCA in pediatric patients have not been established.

8.5 Geriatric Use

Of the total number of subjects in the clinical study of tadalafil for pulmonary arterial hypertension, 28 percent were 65 and over, while 8 percent were 75 and over. No overall differences in safety were observed between subjects over 65 years of age compared to younger subjects or those over 75 years of age. No dose adjustment is warranted based on age alone; however, a greater sensitivity to medications in some older individuals should be considered. [See Clinical Pharmacology (12.3)].

8.6 Renal Impairment

For patients with mild or moderate renal impairment, start ADCIRCA at 20 mg once daily. Increase the dose to 40 mg once daily based upon individual tolerability [see Dosage and Administration (2.2) and Clinical Pharmacology (12.3)].

In patients with severe renal impairment, avoid use of ADCIRCA because of increased tadalafil exposure (AUC), limited clinical experience, and the lack of ability to influence clearance by dialysis [see Clinical Pharmacology (12.3)].

8.7 Hepatic Impairment

Because of limited clinical experience in patients with mild to moderate hepatic cirrhosis (Child-Pugh Class A or B), consider a starting dose of ADCIRCA 20 mg once daily. Patients with severe hepatic cirrhosis (Child-Pugh Class C) have not been studied, thus avoid use of ADCIRCA in such patients [see Dosage and Administration (2.3) and Clinical Pharmacology (12.3)].

10 OVERDOSAGE

Single doses up to 500 mg have been given to healthy male subjects, and multiple daily doses up to 100 mg have been given to male patients with erectile dysfunction. Adverse reactions were similar to those seen at lower doses. Doses greater than 40 mg have not been studied in patients with pulmonary arterial hypertension. In cases of overdose, standard supportive measures should be adopted as needed. Hemodialysis contributes negligibly to tadalafil elimination.

11 DESCRIPTION

ADCIRCA (tadalafil), an oral treatment for pulmonary arterial hypertension, is a selective inhibitor of cyclic guanosine monophosphate (cGMP)–specific phosphodiesterase type 5 (PDE5). Tadalafil has the empirical formula C22H19N3O4 representing a molecular weight of 389.41. The structural formula is:

The chemical designation is pyrazino[1´,2´:1,6]pyrido[3,4–b]indole-1,4-dione, 6-(1,3-benzodioxol-5-yl)-2,3,6,7,12,12a-hexahydro-2-methyl-, (6R,12aR)-. It is a crystalline solid that is practically insoluble in water and very slightly soluble in ethanol.

ADCIRCA is available as orange, film–coated, almond–shaped tablets for oral administration. Each tablet contains 20 mg of tadalafil and the following inactive ingredients: croscarmellose sodium, hydroxypropyl cellulose, hypromellose, iron oxide, lactose monohydrate, magnesium stearate, microcrystalline cellulose, sodium lauryl sulfate, talc, titanium dioxide, and triacetin.

12 CLINICAL PHARMACOLOGY

12.1 Mechanism of Action

Tadalafil is an inhibitor of phosphodiesterase type 5 (PDE5), the enzyme responsible for the degradation of cyclic guanosine monophosphate (cGMP). Pulmonary arterial hypertension is associated with impaired release of nitric oxide by the vascular endothelium and consequent reduction of cGMP concentrations in the pulmonary vascular smooth muscle. PDE5 is the predominant phosphodiesterase in the pulmonary vasculature. Inhibition of PDE5 by tadalafil increases the concentrations of cGMP resulting in relaxation of pulmonary vascular smooth muscle cells and vasodilation of the pulmonary vascular bed.

Studies in vitro have demonstrated that tadalafil is a selective inhibitor of PDE5. PDE5 is found in pulmonary vascular smooth muscle, visceral smooth muscle, corpus cavernosum, skeletal muscle, platelets, kidney, lung, cerebellum, and pancreas.

In vitro studies have shown that the effect of tadalafil is more potent on PDE5 than on other phosphodiesterases. These studies have shown that tadalafil is >10,000–fold more potent for PDE5 than for PDE1, PDE2, PDE4, and PDE7 enzymes, which are found in the heart, brain, blood vessels, liver, leukocytes, skeletal muscle, and other organs. Tadalafil is >10,000–fold more potent for PDE5 than for PDE3, an enzyme found in the heart and blood vessels. Additionally, tadalafil is 700–fold more potent for PDE5 than for PDE6, which is found in the retina and is responsible for phototransduction. Tadalafil is >9,000-fold more potent for PDE5 than for PDE8, PDE9, and PDE10. Tadalafil is 14–fold more potent for PDE5 than for PDE11A1 and 40–fold more potent for PDE5 than for PDE11A4, two of the four known forms of PDE11. PDE11 is an enzyme found in human prostate, testes, skeletal muscle and in other tissues. In vitro, tadalafil inhibits human recombinant PDE11A1 and, to a lesser degree, PDE11A4 activities at concentrations within the therapeutic range. The physiological role and clinical consequence of PDE11 inhibition in humans have not been defined.

12.2 Pharmacodynamics

Effects on Blood Pressure When Administered with Nitrates

In clinical pharmacology studies, tadalafil (5 to 20 mg) was shown to potentiate the hypotensive effect of nitrates. Do not use ADCIRCA in patients taking any form of nitrates [see Contraindications (4.1)].

A double–blind, placebo–controlled, crossover study in 150 male subjects at least 40 years of age (including subjects with diabetes mellitus and/or controlled hypertension) assessed the interaction between nitroglycerin and tadalafil. Subjects received daily doses of tadalafil 20 mg or matching placebo for 7 days and then were given a single dose of 0.4 mg sublingual nitroglycerin (NTG) at pre–specified timepoints following their last dose of tadalafil (2, 4, 8, 24, 48, 72, and 96 hours after tadalafil). A significant interaction between tadalafil and NTG was observed at each timepoint up to and including 24 hours. At 48 hours, by most hemodynamic measures, the interaction between tadalafil and NTG was not observed, although a few more tadalafil subjects compared to placebo experienced greater blood–pressure lowering effects at this timepoint. After 48 hours, the interaction was not detectable. [See Contraindications (4.1)].

Effects on Blood Pressure

The effects of tadalafil on blood pressure alone and administered with antihypertensives, alcohol, and alpha-blockers is shown in Figure 1.

a In some subjects, postural dizziness and orthostatic hypotension were observed. When tadalafil was administered with lower doses of alcohol (0.6 g/kg), hypotension was not observed, and dizziness occurred at a similar frequency to alcohol alone.

b In studies of tadalafil co-administration with doxazosin, the number of subjects with potentially clinically significant standing blood pressure decreases was greater for the combination. Some patients had symptoms associated with the decrease in blood pressure including syncope.

Figure 1: Effects of Tadalafil on Blood Pressure

Effects on Cardiac Electrophysiology

The effect of a single 100 mg dose of tadalafil (2.5 times the recommended dose) on the QT interval was evaluated at the time of peak tadalafil concentration in a randomized, double–blinded, placebo, and active–controlled (intravenous ibutilide) crossover study in 90 healthy males aged 18 to 53 years. The mean change in QTc (Fridericia QT correction) for tadalafil, relative to placebo, was 3.5 milliseconds (two–sided 90% CI=1.9, 5.1). The mean change in QTc (Individual QT correction) for tadalafil, relative to placebo, was 2.8 milliseconds (two–sided 90% CI=1.2, 4.4). In this study, the mean increase in heart rate associated with a 100 mg dose of tadalafil compared to placebo was 3.1 beats per minute.

Effects on Exercise Stress Testing

The effects of tadalafil on cardiac function, hemodynamics, and exercise tolerance were investigated in a single clinical pharmacology study. In this blinded crossover trial, 23 subjects with stable coronary artery disease and evidence of exercise–induced cardiac ischemia were enrolled. The primary endpoint was time to cardiac ischemia. The mean difference in total exercise time was 3 seconds (tadalafil 10 mg minus placebo), which represented no clinically meaningful difference. Further statistical analysis demonstrated that tadalafil was similar to placebo with respect to time to ischemia. Of note, in this study, in some subjects who received tadalafil followed by sublingual nitroglycerin in the post–exercise period, clinically significant reductions in blood pressure were observed, consistent with the augmentation by tadalafil of the blood–pressure–lowering effects of nitrates.

Effects on Vision

Single oral doses of PDE inhibitors have demonstrated transient dose-related impairment of color discrimination (blue/green), using the Farnsworth–Munsell 100–hue test, with peak effects near the time of peak plasma levels. This finding is consistent with the inhibition of PDE6, which is involved in phototransduction in the retina. In a study to assess the effects of a single dose of tadalafil 40 mg on vision (N=59), no effects were observed on visual acuity, intraocular pressure, or pupillometry. Across all clinical studies with tadalafil, reports of changes in color vision were rare (<0.1% of patients).

Effects on Sperm Characteristics

Three studies were conducted in men to assess the potential effect on sperm characteristics of tadalafil 10 mg (one 6-month study) and 20 mg (one 6-month and one 9-month study) administered daily. There were no adverse effects on sperm morphology or sperm motility in any of the three studies. In the study of 10 mg tadalafil for 6 months and the study of 20 mg tadalafil for 9 months, results showed a decrease in mean sperm concentrations relative to placebo, although these differences were not clinically meaningful. This effect was not seen in the study of 20 mg tadalafil taken for 6 months. In addition there was no adverse effect on mean concentrations of reproductive hormones, testosterone, luteinizing hormone or follicle stimulating hormone with either 10 or 20 mg of tadalafil compared to placebo.

Dose-Response Relationship

Dose-response relationships, between 20 mg and 40 mg, were not observed for 6-minute walk distance or pulmonary vascular resistance (PVR) in subjects with PAH in the placebo-controlled study. Median change from baseline in 6-minute walk distance was 32 meters and 35 meters at 16 weeks in subjects receiving 20 mg and 40 mg daily, respectively. Mean change from baseline PVR was -254 dynes*sec*cm^-5 and -209 dynes*sec*cm^-5 at 16 weeks in patients receiving 20 mg and 40 mg daily, respectively.

12.3 Pharmacokinetics

Over a dose range of 2.5 to 20 mg, tadalafil exposure (AUC) increases proportionally with dose in healthy subjects. In PAH patients administered between 20 and 40 mg of tadalafil, an approximately 1.5-fold greater AUC was observed indicating a less than proportional increase in exposure over the entire dose range of 2.5 to 40 mg. During tadalafil 20 and 40 mg once daily dosing, steady-state plasma concentrations were attained within 5 days, and exposure was approximately 1.3-fold higher than after a single dose.

Absorption — After single oral-dose administration, the maximum observed plasma concentration (Cmax) of tadalafil is achieved between 2 and 8 hours (median time of 4 hours). Absolute bioavailability of tadalafil following oral dosing has not been determined.

The rate and extent of absorption of tadalafil are not influenced by food; thus ADCIRCA may be taken with or without food.

Distribution — The mean apparent volume of distribution following oral administration is approximately 77 L, indicating that tadalafil is distributed into tissues. At therapeutic concentrations, 94% of tadalafil in plasma is bound to proteins.

Metabolism — Tadalafil is predominantly metabolized by CYP3A to a catechol metabolite. The catechol metabolite undergoes extensive methylation and glucuronidation to form the methylcatechol and methylcatechol glucuronide conjugate, respectively. The major circulating metabolite is the methylcatechol glucuronide. Methylcatechol concentrations are less than 10% of glucuronide concentrations. In vitro data suggests that metabolites are not expected to be pharmacologically active at observed metabolite concentrations.

Elimination — Following 40 mg, the mean oral clearance for tadalafil is 3.4 L/hr and the mean terminal half-life is 15 hours in healthy subjects. In patients with pulmonary hypertension not receiving concomitant bosentan, the mean oral clearance for tadalafil is 1.6 L/hr, and the mean terminal half-life is 35 hours. Tadalafil is excreted predominantly as metabolites, mainly in the feces (approximately 61% of the dose) and to a lesser extent in the urine (approximately 36% of the dose).

Population pharmacokinetics — In patients with pulmonary hypertension not receiving concomitant bosentan, the average tadalafil exposure at steady-state following 40 mg was 26% higher when compared to those of healthy volunteers. The results suggest a lower clearance of tadalafil in patients with pulmonary hypertension compared to healthy volunteers.

Geriatric patients

In healthy male elderly subjects (65 years or over) after a 10 mg dose, a lower oral clearance of tadalafil, resulting in 25% higher exposure (AUC) with no effect on Cmax was observed relative to that in healthy subjects 19 to 45 years of age.

Renal impairment

In clinical pharmacology studies using single-dose tadalafil (5 to 10 mg), tadalafil exposure (AUC) doubled in subjects with mild (creatinine clearance 51 to 80 mL/min) or moderate (creatinine clearance 31 to 50 mL/min) renal impairment. In subjects with end-stage renal disease on hemodialysis, there was a two-fold increase in Cmax and 2.7- to 4.1-fold increase in AUC following single-dose administration of 10 or 20 mg tadalafil, respectively. Exposure to total methylcatechol (unconjugated plus glucuronide) was 2- to 4-fold higher in subjects with renal impairment, compared to those with normal renal function. Hemodialysis (performed between 24 and 30 hours post-dose) contributed negligibly to tadalafil or metabolite elimination [see Dosage and Administration (2.2)].

Hepatic impairment

In clinical pharmacology studies, tadalafil exposure (AUC) in subjects with mild or moderate hepatic impairment (Child-Pugh Class A or B) was comparable to exposure in healthy subjects when a dose of 10 mg was administered. There are no available data for doses higher than 10 mg of tadalafil in patients with hepatic impairment. Insufficient data are available for subjects with severe hepatic impairment (Child-Pugh Class C) [see Dosage and Administration (2.3)].

Patients with diabetes mellitus

In male patients with diabetes mellitus after a 10 mg tadalafil dose, exposure (AUC) was reduced approximately 19% and Cmax was 5% lower than that observed in healthy subjects. No dose adjustment is warranted.

Race

Pharmacokinetic studies have included subjects from different ethnic groups, and no differences in the typical exposure to tadalafil have been identified. No dose adjustment is warranted.

Gender

In healthy female and male subjects following single and multiple-doses of tadalafil, no clinically relevant differences in exposure (AUC and Cmax) were observed. No dose adjustment is warranted.

Drug interaction studies

Tadalafil is a substrate of and predominantly metabolized by CYP3A.

Cytochrome P450 3A4 inhibitors

Ketoconazole increased tadalafil exposure relative to the values for tadalafil alone (Figure 2). Although specific interactions have not been studied, other CYP3A inhibitors, such as erythromycin, itraconazole, and grapefruit juice, would likely increase tadalafil exposure.

Ritonavir

Ritonavir increased tadalafil 20–mg single-dose exposure relative to the values for tadalafil alone. Ritonavir inhibits and induces CYP3A, the enzyme involved in the metabolism of tadalafil, in a time-dependent manner. The initial inhibitory effect of ritonavir on CYP3A may be mitigated by a more slowly evolving induction effect so that after about 1 week of ritonavir twice daily, the exposure of tadalafil is similar in the presence of and absence of ritonavir [see Dosage and Administration (2.4) and Drug Interactions (7.5)]. Although specific interactions have not been studied, other HIV protease inhibitors would likely increase tadalafil exposure.

Cytochrome P450 3A4 inducers

Rifampin (600 mg daily), a CYP3A inducer, reduced tadalafil 10 mg single–dose exposure (AUC) by 88% and Cmax by 46%, relative to the values for tadalafil 10 mg alone [see Drug Interactions (7.5)].

Bosentan, a substrate of CYP2C9 and CYP3A and a moderate inducer of CYP3A, CYP2C9 and possibly CYP2C19, reduced tadalafil systemic exposure following multiple-dose co-administration (Figure 2). Although specific interactions have not been studied, other CYP3A inducers, such as carbamazepine, phenytoin, and phenobarbital, would likely decrease tadalafil exposure.

Exposure changes of tadalafil following co-administration with other drugs are shown in Figure 2.

a Ritonavir is also a CYP2C9/CYP2C19/CYP2D6 Inhibitor and CYP3A inducer.

b [see Dosage and Administration (2.4)].

c Bosentan is also a CYP2C9/CYP2C19 inducer.

Figure 2: Impact of Other Drugs on the Pharmacokinetics of Tadalafil

Cytochrome P450 substrates

Tadalafil is not expected to cause clinically significant inhibition or induction of the clearance of drugs metabolized by cytochrome P450 (CYP) isoforms.

Exposure changes of drugs following co-administration with tadalafil are shown in Figure 3.

a A small augmentation (increase of 3 beats per minute) in heart rate was observed with theophylline.

b Tadalafil (40 mg qd) had no clinically significant effect on exposure (AUC and Cmax) of bosentan metabolites.

c 95% CI

Figure 3: Impact of Tadalafil on the Pharmacokinetics of Other Drugs

13 NONCLINICAL TOXICOLOGY

13.1 Carcinogenesis, Mutagenesis, Impairment of Fertility

Carcinogenesis — Tadalafil was not carcinogenic to rats or mice when administered daily for 2 years at doses up to 400 mg/kg/day. Systemic drug exposures, as measured by AUC of unbound tadalafil, were approximately 5–fold for mice, and 7– and 14–fold for male and female rats, respectively, the exposures at the maximum recommended human dose (MRHD) of 40 mg.

Mutagenesis — Tadalafil was not mutagenic in the in vitro bacterial Ames assays or the forward mutation test in mouse lymphoma cells. Tadalafil was not clastogenic in the in vitro chromosomal aberration test in human lymphocytes or the in vivo rat micronucleus assays.

Impairment of Fertility — There were no effects on fertility, reproductive performance or reproductive organ morphology in male or female rats given oral doses of tadalafil up to 400 mg/kg/day, a dose producing AUCs for unbound tadalafil of 6–fold for males or 17–fold for females the exposures at the MRHD of 40 mg. In beagle dogs given tadalafil daily for 3 to 12 months, there was treatment–related non–reversible degeneration and atrophy of the seminiferous tubular epithelium in the testes in 20–100% of the dogs that resulted in a decrease in spermatogenesis in 40–75% of the dogs at doses of ≥10 mg/kg/day. Systemic exposure (based on AUC) at no–observed–adverse-effect–level (NOAEL) (10 mg/kg/day) for unbound tadalafil was similar to that expected in humans at the MRHD of 40 mg.

There were no treatment–related testicular findings in rats or mice treated with doses up to 400 mg/kg/day for 2 years.

13.2 Animal Toxicology and/or Pharmacology

Animal studies showed vascular inflammation in tadalafil–treated mice, rats, and dogs. In mice and rats, lymphoid necrosis and hemorrhage were seen in the spleen, thymus, and mesenteric lymph nodes at unbound tadalafil exposure of 1– to 17–fold the human exposure (AUCs) at the MRHD of 40 mg. In dogs, an increased incidence of disseminated arteritis was observed in 1– and 6-month studies at unbound tadalafil exposure of 0.5– to 38–fold the human exposure (AUC) at the MRHD of 40 mg. In a 12–month dog study, no disseminated arteritis was observed, but 2 dogs exhibited marked decreases in white blood cells (neutrophils) and moderate decreases in platelets with inflammatory signs at unbound tadalafil exposures of approximately 4– to 10–fold the human exposure at the MRHD of 40 mg. The abnormal blood–cell findings were reversible within 2 weeks upon removal of the drug.

14 CLINICAL STUDIES

14.1 ADCIRCA for Pulmonary Arterial Hypertension

A randomized, double-blind, 16 week placebo-controlled study was conducted in 405 patients with pulmonary arterial hypertension, defined as a resting mean pulmonary artery pressure (mPAP) ≥25 mm Hg, pulmonary capillary wedge pressure (PCWP) ≤15 mm Hg, and pulmonary vascular resistance (PVR) ≥3 Wood units via right heart catheterization. Allowed background therapy included bosentan (maintenance dosing up to 125 mg twice daily) and chronic anticoagulation. The use of prostacyclin or analogue, L–arginine, phosphodiesterase inhibitor, or other chronic PAH medications were not permitted.

Subjects were randomly assigned to 1 of 5 treatment groups (tadalafil 2.5, 10, 20, 40 mg, or placebo) in a 1:1:1:1:1 ratio. Subjects had to be at least 12 years of age and had a diagnosis of PAH that was idiopathic, heritable, related to connective tissue disease, anorexigen use, human immunodeficiency virus (HIV) infection, associated with an atrial-septal defect, or associated with surgical repair of a congenital systemic-to-pulmonary shunt of least 1 year in duration (for example, ventricular septal defect, patent ductus arteriosus). Patients with a history of left-sided heart disease, severe renal insufficiency, or pulmonary hypertension related to conditions other than specified in the inclusion criteria were not eligible for enrollment.

The mean age of all subjects was 54 years (range 14 - 90 years) with the majority of subjects being Caucasian (81%) and female (78%). PAH etiologies were predominantly idiopathic or heritable PAH (61%) and related to connective tissue disease (23%). More than half (53%) of the subjects in the study were receiving concomitant bosentan therapy. The majority of subjects had a World Health Organization (WHO) Functional Class III (65%) or II (32%). The mean baseline 6-minute walk distance (6-MWD) was 343 meters. Of the 405 subjects, 341 completed the study.

The primary efficacy endpoint was the change from baseline at week 16 in 6-MWD (see Figure 4). In the ADCIRCA 40 mg treatment group, the placebo-adjusted mean change increase in 6-MWD was 33 meters (95% C.I. 15-50 meters; p=0.0004). The improvement in 6-MWD was apparent at 8 weeks of treatment and then maintained at week 12 and week 16.

Figure 4: 6-Minute Walk Distance (meters) Mean Change from Baseline, with 95% Confidence Intervals

Placebo-adjusted changes in 6-MWD at 16 weeks were evaluated in subgroups (see Figure 5). In patients taking only ADCIRCA 40 mg (i.e., without concomitant bosentan), the placebo-adjusted mean change in 6-MWD was 44 meters. In patients taking ADCIRCA 40 mg and concomitant bosentan therapy, the placebo adjusted mean change in 6-MWD was 23 meters.

Figure 5: Placebo-adjusted Mean Change in 6-Minute Walk Distance (meters) of ADCIRCA 40 mg, with 95% Confidence Intervals

There was less clinical worsening (defined as death, lung transplantation, atrial septostomy, hospitalization because of worsening PAH, initiation of new PAH therapy [prostacyclin or analog, endothelin receptor antagonist, PDE5 inhibitor], or worsening WHO functional class) in the ADCIRCA 40 mg group compared to the placebo group and the groups that used lower doses of ADCIRCA.

Table 2: Number (percent) with Clinical Worseninga
 |  | ADCIRCA
 | Placebo N=82 | 2.5 mg N=82 | 10 mg N=80 | 20 mg N=82 | 40 mg N=79
Total with clinical worsening | 13 (16) | 10 (12) | 7 (9) | 8 (10) | 4 (5)
Death | 1 | 0 | 1 | 0 | 0
Hospitalization for worsening PAH | 2 | 2 | 3 | 0 | 1
New PAH therapy | 0 | 1 | 0 | 2 | 1
Worsening WHO class | 11 | 10 | 6 | 6 | 3
a Subjects may be counted in more than one category

The Kaplan-Meier plot of times to clinical worsening is shown below in Figure 6.

Figure 6: Kaplan-Meier Plot of Time to Clinical Worsening

14.2 Long-Term Treatment of Pulmonary Arterial Hypertension

Patients (N=357) from the placebo-controlled study entered a long-term extension study. Of these, 311 patients have been treated with tadalafil for at least 6 months and 182 for 1 year (median exposure 356 days; range 2 days to 415 days). The survival rate in the extension study was 96.5 per 100 patient years. Without a control group, these data must be interpreted cautiously.

16 HOW SUPPLIED/STORAGE AND HANDLING

16.1 How Supplied

ADCIRCA (tadalafil) is supplied as follows:

20 mg orange, film–coated, almond–shaped tablets (not scored), debossed with “4467”

Bottles of 60 NDC 66302-467-60

16.2 Storage

Store at 25°C (77°F): excursions permitted to 15–30°C (59–86°F) [see USP Controlled Room Temperature].

Keep out of reach of children.

17 PATIENT COUNSELING INFORMATION

See FDA-Approved Patient Labeling (Patient Information)

- Inform patients of contraindication of ADCIRCA with any use of organic nitrates or GC stimulators.
- Inform patients that tadalafil is also marketed as CIALIS for erectile dysfunction (ED) and for the signs and symptoms of benign prostatic hyperplasia (BPH). Advise patients taking ADCIRCA not to take CIALIS or other PDE5 inhibitors.
- Advise patients to seek immediate medical attention in the event of a sudden loss of vision in one or both eyes while taking ADCIRCA. Such an event may be a sign of NAION. Also discuss with patients that there is an increased risk of NAION in individuals who have already experienced NAION in one eye, including whether such individuals could be adversely affected by use of vasodilators such as PDE5 inhibitors.
- Advise patients to seek prompt medical attention in the event of sudden decrease or loss of hearing while taking ADCIRCA. These events may be accompanied by tinnitus and dizziness.

Manufactured by: Eli Lilly and Company, Indianapolis, IN 46285, USA

Marketed by: United Therapeutics Corporation

Copyright © 2009, 2020, Eli Lilly and Company. All rights reserved.

ADC-0005-USPI-20200915

PATIENT INFORMATION

ADCIRCA® (Ad-sur-kuh)

(tadalafil) tablets

Read this patient information before you start taking ADCIRCA and each time you get a refill. There may be new information. This information does not take the place of talking with your healthcare provider about your medical condition or treatment.

What is the most important information I should know about ADCIRCA?

Never take ADCIRCA with any nitrate or guanylate cyclase stimulator medicines:

- Your blood pressure could drop quickly to an unsafe level
- You could get dizzy, faint and even have a heart attack or stroke.

Nitrates include:

- Medicines that treat chest pain (angina)
- Nitroglycerin in any form including tablets, patches, sprays, and ointments
- Other nitrate medicines (isosorbide mononitrate or dinitrate)
- Street drugs that are inhaled, called “poppers” (amyl nitrate, butyl nitrate or nitrite)

Guanylate cyclase stimulators include:

- Riociguat (Adempas®) a medicine that treats pulmonary arterial hypertension and chronic-thromboembolic pulmonary hypertension

Ask your healthcare provider or pharmacist if you are not sure if you take a nitrate or guanylate cyclase stimulator medicine.

What is ADCIRCA?

ADCIRCA is a prescription medicine used to treat pulmonary arterial hypertension (PAH, high blood pressure in your lungs) to improve your ability to exercise.

It is not known if ADCIRCA is safe or effective in children.

Who should not take ADCIRCA?

Do not take ADCIRCA if you

- take any medicines called nitrates.
- use recreational drugs called “poppers” like amyl nitrate, butyl nitrate or nitrite.
- take any medicines called guanylate cyclase stimulators
- are allergic to tadalafil or any other ingredient in ADCIRCA. See “What are the ingredients in ADCIRCA?” at the end of this leaflet.

See “What is the most important information I should know about ADCIRCA?”

What should I tell my healthcare provider before taking ADCIRCA?

Before taking ADCIRCA, tell your healthcare provider about all of your medical conditions, including if you:

- are allergic to ADCIRCA or Cialis or any of its ingredients. See the end of this leaflet for a complete list of ingredients in ADCIRCA.
- have pulmonary veno-occlusive disease (PVOD)
- have heart problems
- have low blood pressure
- have liver problems
- have kidney problems or get dialysis
- have retinitis pigmentosa, a rare genetic eye disease
- have ever had any sudden vision loss, including any damage to your optic nerve or NAION.
- have ever had hearing problems such as ringing in the ears, dizziness, or loss of hearing
- have a deformed penis shape or Peyronie's disease
- have had an erection that lasted more than 4 hours
- have blood cell problems such as sickle cell anemia, multiple myeloma, or leukemia
- are pregnant or planning to become pregnant. Talk to your healthcare provider if you are pregnant or plan to become pregnant.
- are breastfeeding or plan to breast feed. If you breastfeed while taking ADCIRCA, it is likely that ADCIRCA will pass into your breast milk. You and your healthcare provider should decide if you will take ADCIRCA or breastfeed. You should not do both.

Tell your healthcare provider about all the medicines you take, including prescription and non-prescription medicines, vitamins, and herbal supplements. ADCIRCA and other medicines may affect each other.

Especially tell your healthcare provider if you take any of these medicines*:

- nitrates or guanylate cyclase stimulators (see “What is the most important information I should know about ADCIRCA?”)
- alpha blockers, used to treat prostate disease and high blood pressure. Your blood pressure could suddenly drop. You could get dizzy or faint.
- protease inhibitors, used to treat HIV infection, such as ritonavir (Norvir®, Kaletra®)
- ketoconazole (Extina®, Xolegel®, Ketozole®, Nizoral A-D®, Nizoral®) itraconazole (Sporanox®)
- erythromycin (several brand names exist. Please consult your healthcare provider to determine if you are taking this medicine)
- rifampin (Rifadin®, Rifamate®, Rifater®, Rimactane®)
- bosentan (Tracleer®)
- phenobarbital, phenytoin (Dilantin®), carbamazepine (Tegretol®)
- CIALIS® or other medicines or treatments for erectile dysfunction (impotence).
- ADCIRCA is also marketed as CIALIS for the treatment of male erectile dysfunction (ED, impotence) and for the signs and symptoms of benign prostatic hyperplasia (BPH, enlarged prostate). Do not take both ADCIRCA and CIALIS. Do not take ADCIRCA and other medicines or treatments for erectile dysfunction.

Ask your healthcare provider or pharmacist for a list of these medicines, if you are not sure.

Know the medicines you take. Keep a list of them and show it to your healthcare provider and pharmacist when you get a new medicine.

How should I take ADCIRCA?

- Take ADCIRCA exactly as your healthcare provider tells you.
- Take ADCIRCA tablets at the same time every day. You should take both tablets at the same time, one after the other, every day. Do not split your dose.
- ADCIRCA can be taken with or without food.
- Do not change your dose or stop taking ADCIRCA without speaking to your healthcare provider.
- If you take too much ADCIRCA, call your healthcare provider or go to an emergency department right away.

What should I avoid while taking ADCIRCA?

Do not have more than 4 alcohol-containing drinks in a short period of time while you take ADCIRCA. Drinking too much alcohol can lower your blood pressure. You could get dizzy or faint.

What are the possible side effects of ADCIRCA?

The following side effects were reported rarely in patients taking tadalafil:

- Decreased eyesight or loss of vision in one or both eyes (NAION). If you notice a sudden decrease or loss of vision in one or both eyes, contact a healthcare provider right away.
- Sudden decrease or loss of hearing, sometimes with ringing in the ears and dizziness. If you notice a sudden decrease or loss of hearing, contact a healthcare provider right away.
- In men, an erection that lasts more than 4 hours (with or without pain). Talk to your healthcare provider or go to the emergency department right away. An erection that lasts more than 4 hours must be treated as soon as possible or you can have lasting damage to your penis, including the inability to have erections.

See “What is the most important information I should know about ADCIRCA?”

The most common side effects with ADCIRCA include:

- headache
- muscle pain
- getting red or hot in the face (flushing)
- nausea
- pain in the arms, legs, or back
- upset stomach
- stuffy or congested nose

Tell your healthcare provider about any side effect that bothers you or does not go away.

These are not all the possible side effects of ADCIRCA. For more information, ask your healthcare provider or pharmacist. Call your doctor for medical advice about side effects. You may report side effects to FDA at 1-800-FDA-1088.

How Should I Store ADCIRCA?

Store ADCIRCA at room temperature between 59° and 86°F (15° and 30°C).

Keep ADCIRCA and all medicines out of the reach of children.

General Information about the safe and effective use of ADCIRCA

Medicines are sometimes prescribed for conditions that are not mentioned in patient information leaflets. Do not use ADCIRCA for a condition for which it was not prescribed. Do not give ADCIRCA to other people, even if they have the same symptoms you have. It may harm them.

This patient information leaflet summarizes the most important information about ADCIRCA. If you would like more information, talk with your healthcare provider. You can ask your healthcare provider or pharmacist for information about ADCIRCA that is written for healthcare professionals. For more information, go to www.ADCIRCA.com or call 1-800-LILLYRX (1-800-545-5979).

What Are The Ingredients In ADCIRCA?

Active Ingredient: tadalafil

Inactive Ingredients: croscarmellose sodium, hydroxypropyl cellulose, hypromellose, iron oxide, lactose monohydrate, magnesium stearate, microcrystalline cellulose, sodium lauryl sulfate, talc, titanium dioxide, and triacetin.

Rx only

ADCIRCA® (tadalafil) is a trademark of Eli Lilly and Company.

*The brands listed are trademarks of their respective owners and are not trademarks of Eli Lilly and Company. The makers of these brands are not affiliated with and do not endorse Eli Lilly and Company or its products.

Revised 09/2020

Manufactured by: Eli Lilly and Company, Indianapolis, IN 46285, USA

Marketed by: United Therapeutics Corporation

Copyright © 2009, 2020, Eli Lilly and Company. All rights reserved.

ADC-0004-PPI-20200915

PACKAGE LABEL – ADCIRCA 20 mg

60 tablets

NDC 66302-467-60

Rx only

TA 4467

adcirca®

tadalafil tablets

20 mg 4467

United Therapeutics Corporation

Lilly

Same active ingredient as Cialis